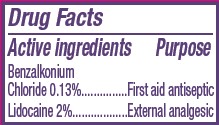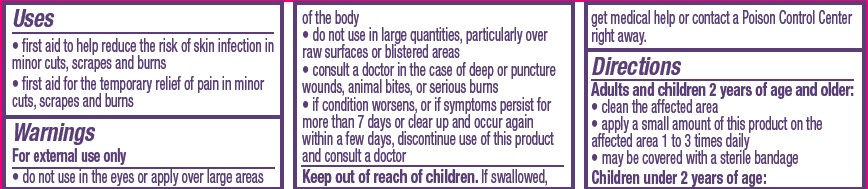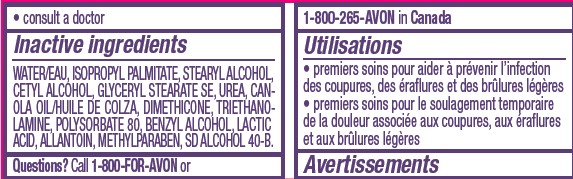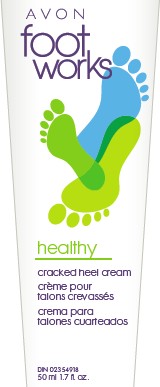 DRUG LABEL: Foot Works
NDC: 10096-4423 | Form: CREAM
Manufacturer: Avon Products, Inc.
Category: otc | Type: HUMAN OTC DRUG LABEL
Date: 20120530

ACTIVE INGREDIENTS: LIDOCAINE 1 mL/50 mL; BENZALKONIUM CHLORIDE 0.065 mL/50 mL

Drug Facts

Active ingredients
Benzalkonium Chloride 0.13%.......
Lidocaine 2%.........

Purpose
........First aid antiseptic
...........External analgesic

Uses
• first aid to help reduce the risk of skin infection in minor cuts, scrapes and burns
• first aid for the temporary relief of pain in minor cuts, scrapes and burns

Warnings
For external use only
• do not use in the eyes or apply over large areas of the body
• do not use in large quantities, particularly over raw surfaces or blistered areas
• consult a doctor in the case of deep or puncture wounds, animal bites, or serious burns
• if condition worsens, or if symptoms persist for more than 7 days or clear up and occur again within a few days, discontinue use of this product and consult a doctor

Keep out of reach of children. If swallowed, get medical help or contact a Poison Control Center right away.

Directions
Adults and children 2 years of age and older:
• clean the affected area
• apply a small amount of this product on the affected area 1 to 3 times daily
• may be covered with a sterile bandage
Children under 2 years of age:
• consult a doctor

Inactive ingredients
WATER/EAU, ISOPROPYL PALMITATE, STEARYL ALCOHOL, CETYL ALCOHOL, GLYCERYL STEARATE SE, UREA, CANOLA OIL/HUILE DE COLZA, DIMETHICONE, TRIETHANOLAMINE, POLYSORBATE 80, BENZYL ALCOHOL, LACTIC ACID, ALLANTOIN, METHYLPARABEN, SD ALCOHOL 40-B.

QUESTIONS

Questions? Call 1-800-FOR-AVON or 1-800-265-AVON in Canada